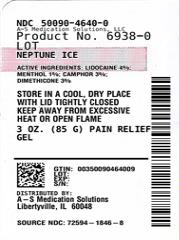 DRUG LABEL: Neptune Ice
NDC: 50090-4640 | Form: GEL
Manufacturer: A-S Medication Solutions
Category: otc | Type: HUMAN OTC DRUG LABEL
Date: 20210614

ACTIVE INGREDIENTS: CAMPHOR (NATURAL) 0.0291 g/1 mL; DIMETHICONE 0.0291 g/1 mL; LIDOCAINE 0.0388 g/1 mL; MENTHOL 0.0097 g/1 mL
INACTIVE INGREDIENTS: ALOE VERA LEAF; POLYSORBATE 20; FD&C BLUE NO. 1; ETHYLHEXYLGLYCERIN; ARNICA MONTANA FLOWER; PHENOXYETHANOL; CARBOXYPOLYMETHYLENE; INDIAN FRANKINCENSE OIL; WATER; DIMETHYL SULFONE; ALCOHOL; TROLAMINE; SORBITOL

Neptune Ice

Methemoglobinemia

Cases of methemoglobinemia have been reported in association with local anesthetic use. Although all patients are at risk for methemoglobinemia, patients with glucose-6-phosphate dehydrogenase deficiency, congenital or idiopathic methemoglobinemia, cardiac or pulmonary compromise, infants under 6 months of age, and concurrent exposure to oxidizing agents or their metabolites are more susceptible to developing clinical manifestations of the condition. If local anesthetics must be used in these patients, close monitoring for symptoms and signs of methemoglobinemia is recommended.

Signs and symptoms of methemoglobinemia may occur immediately or may be delayed some hours after exposure and are characterized by a cyanotic skin discoloration and abnormal coloration of the blood. Methemoglobin levels may continue to rise; therefore, immediate treatment is required to avert more serious central nervous system and cardiovascular adverse effects, including seizures, coma, arrhythmias, and death. Discontinue lidocaine-containing products and any other oxidizing agents. Depending on the severity of the symptoms, patients may respond to supportive care, i.e., oxygen therapy, hydration. More severe symptoms may require treatment with methylene blue, exchange transfusion, or hyperbaric oxygen

Active Ingredient

Lidocaine 4%

Purpose

Topical Anesthetic

Active Ingredient

Menthol 1%

Purpose

Topical Analgesic

Active Ingredient

Camphor 3%

Purpose

Topical Analgesic

Active Ingredient

Dimethicone 3%

Purpose

Skin Conditioner

Uses:

For the temporary relief of joint pain and muscle pain associated with:

- Arthritis
- Backache
- Discomfort
- Cramps
- Neckache
- Soreness
- Sprains
- Strains

Warnings

For External Use Only

Flammable

Keep away from excessive heat or open flame

Do Not Use

- On damaged or irritated skin
- With a bandage or heating pad
- If you are allergic to any ingredients in this product
- Other than as directed

When Using This Product

Avoid contact with the eyes

Stop Use and Ask a Doctor If

- Condition worsens
- Excessive skin irritation develops
- Symptoms persist for more than 7 days, or symptoms clear up and occur again within 3 days

If You Are Pregnant or Breast Feeding

Ask a health professional before use

Keep Out of Reach of Children

If ingested, seek medical help or contact a Poison Control Center immediately

Directions

Adults and Children 12 years of Age and Older:

- Clean and dry the affected area
- Apply product directly to your skin, up to 4 times daily

Other Information

- Store in a cool, dry place with lid tightly closed

Inactive Ingredients

Aloe Barbadensis Leaf Juice, Arnica Montana Flower, Boswellia Serrata Extract, Carbomer, Ethylhexylglycerin, FD&C Blue #1, Methylsulfonylmethane, Phenoxyethanol, Polysorbate 20, SD-Alcohol 40B, Sorbitol, Triethanolamine, Water.

Questions or Comments?

(877) 985-8377

HOW SUPPLIED

Product: 50090-4640

NDC: 50090-4640-0 89 mL in a TUBE, WITH APPLICATOR